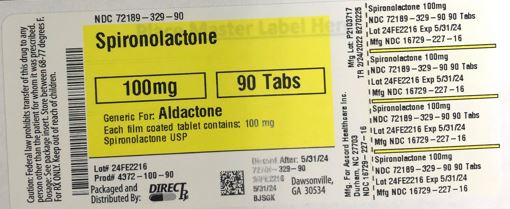 DRUG LABEL: SPIRONOLACTONE
NDC: 72189-329 | Form: TABLET, FILM COATED
Manufacturer: Direct Rx
Category: prescription | Type: HUMAN PRESCRIPTION DRUG LABEL
Date: 20220228

ACTIVE INGREDIENTS: SPIRONOLACTONE 100 mg/1 1
INACTIVE INGREDIENTS: DIBASIC CALCIUM PHOSPHATE DIHYDRATE; SILICON DIOXIDE; HYPROMELLOSES; POLYETHYLENE GLYCOL 400; POVIDONE K25; FERRIC OXIDE RED; LACTOSE MONOHYDRATE; PEPPERMINT OIL; TALC; STARCH, CORN; MAGNESIUM STEARATE; FERRIC OXIDE YELLOW

SPIRONOLACTONE

INDICATIONS AND USAGE

1.1 Heart Failure

Spironolactone tablets are indicated for treatment of NYHA Class III–IV heart failure and reduced ejection fraction to increase survival, manage edema, and reduce the need for hospitalization for heart failure.

Spironolactone tablets are usually administered in conjunction with other heart failure therapies.

1.2 Hypertension

Spironolactone tablets are indicated as add-on therapy for the treatment of hypertension, to lower blood pressure in patients who are not adequately controlled on other agents. Lowering blood pressure reduces the risk of fatal and nonfatal cardiovascular events, primarily strokes and myocardial infarctions. These benefits have been seen in controlled trials of antihypertensive drugs from a wide variety of pharmacologic classes.

Control of high blood pressure should be part of comprehensive cardiovascular risk management, including, as appropriate, lipid control, diabetes management, antithrombotic therapy, smoking cessation, exercise, and limited sodium intake. Many patients will require more than one drug to achieve blood pressure goals. For specific advice on goals and management, see published guidelines, such as those of the National High Blood Pressure Education Program's Joint National Committee on Prevention, Detection, Evaluation, and Treatment of High Blood Pressure (JNC).

Numerous antihypertensive drugs, from a variety of pharmacologic classes and with different mechanisms of action, have been shown in randomized controlled trials to reduce cardiovascular morbidity and mortality, and it can be concluded that it is blood pressure reduction, and not some other pharmacologic property of the drugs, that is largely responsible for those benefits. The largest and most consistent cardiovascular outcome benefit has been a reduction in the risk of stroke, but reductions in myocardial infarction and cardiovascular mortality also have been seen regularly.

Elevated systolic or diastolic pressure causes increased cardiovascular risk, and the absolute risk increase per mmHg is greater at higher blood pressures, so that even modest reductions of severe hypertension can provide substantial benefit. Relative risk reduction from blood pressure reduction is similar across populations with varying absolute risk, so the absolute benefit is greater in patients who are at higher risk independent of their hypertension (for example, patients with diabetes or hyperlipidemia), and such patients would be expected to benefit from more aggressive treatment to a lower blood pressure goal.

Some antihypertensive drugs have smaller blood pressure effects (as monotherapy) in black patients, and many antihypertensive drugs have additional approved indications and effects (e.g., on angina, heart failure, or diabetic kidney disease). These considerations may guide selection of therapy.

1.3 Edema Associated with Hepatic Cirrhosis or Nephrotic Syndrome

Spironolactone tablets are indicated for the management of edema in the following settings:

Cirrhosis of the liver when edema is not responsive to fluid and sodium restriction.
Nephrotic syndrome when treatment of the underlying disease, restriction of fluid and sodium intake, and the use of other diuretics produce an inadequate response.

Because it increases serum potassium, spironolactone tablets may be useful for treating edema when administration of other diuretics has caused hypokalemia.

1.4 Primary Hyperaldosteronism

Spironolactone tablets are indicated in the following settings:

Short-term preoperative treatment of patients with primary hyperaldosteronism.
Long-term maintenance therapy for patients with discrete aldosterone-producing adrenal adenomas who are not candidates for surgery.
Long-term maintenance therapy for patients with bilateral micro or macronodular adrenal hyperplasia (idiopathic hyperaldosteronism).

DOSAGE FORMS AND STRENGTHS

Spironolactone tablets USP 25 mg are light yellow to yellow colored, round, biconvex, film coated tablets with inscription “AD” on one side and plain on the other side having faint odour of peppermint.

Spironolactone tablets USP 50 mg are light orange to orange colored, oval, biconvex, film coated tablets with inscription “AE” on one side and breakline on the other side having faint odour of peppermint.

Spironolactone tablets USP 100 mg are light peach to peach colored, round, biconvex, film coated tablets with inscription “AF” on one side and breakline on the other side having faint odour of peppermint.

CONTRAINDICATIONS

Spironolactone tablets are contraindicated in the patients with:

Hyperkalemia
Addison's disease
Concomitant use of eplerenone

DESCRIPTION

Spironolactone oral tablets USP, for oral administration contain 25 mg, 50 mg, or 100 mg of the aldosterone antagonist spironolactone, 17-hydroxy-7α-mercapto-3-oxo-17α-pregn-4-ene-21-carboxylic acid γ-lactone acetate, which has the following structural formula:

Chemical Structure
Spironolactone is practically insoluble in water, soluble in alcohol, and freely soluble in benzene and in chloroform.

Inactive ingredients include lactose monohydrate, dibasic calcium phosphate, povidone, peppermint oil, purified talc, pregelatinised starch, colloidal anhydrous silica, magnesium stearate, hypromellose, polyethylene glycol 400, titanium dioxide and iron oxide yellow. In addition iron oxide red (50 mg and 100 mg tablets) is included in the film coating of specific strengths.

HOW SUPPLIED

Spironolactone tablets USP 25 mg tablets are Light yellow to yellow colored, round, biconvex, film coated tablets with inscription “AD” on one side and plain on the other side having faint odour of peppermint, supplied as:
NDC Number Size
16729-225-01 bottle of 100 with a child-resistant closure
16729-225-16 bottle of 500
16729-225-17 bottle of 1,000
16729-225-19 bottle of 2,500
Spironolactone tablets USP 50 mg tablets are Light orange to orange colored, oval, biconvex, film coated tablets with inscription “AE” on one side and breakline on the other side having faint odour of peppermint, supplied as:
NDC Number Size
16729-226-01 bottle of 100 with a child-resistant closure
16729-226-16 bottle of 500
Spironolactone tablets USP 100 mg tablets are Light peach to peach colored, round, biconvex, film coated tablets with inscription “AF” on one side and breakline on the other side having faint odour of peppermint, supplied as:
NDC Number Size
16729-227-01 bottle of 100 with a child-resistant closure
16729-227-16 bottle of 500
Store at 20° to 25°C (68° to 77°F) [See USP Controlled Room Temperature] Protect from light. Dispense in tight, Light-resistant containers.